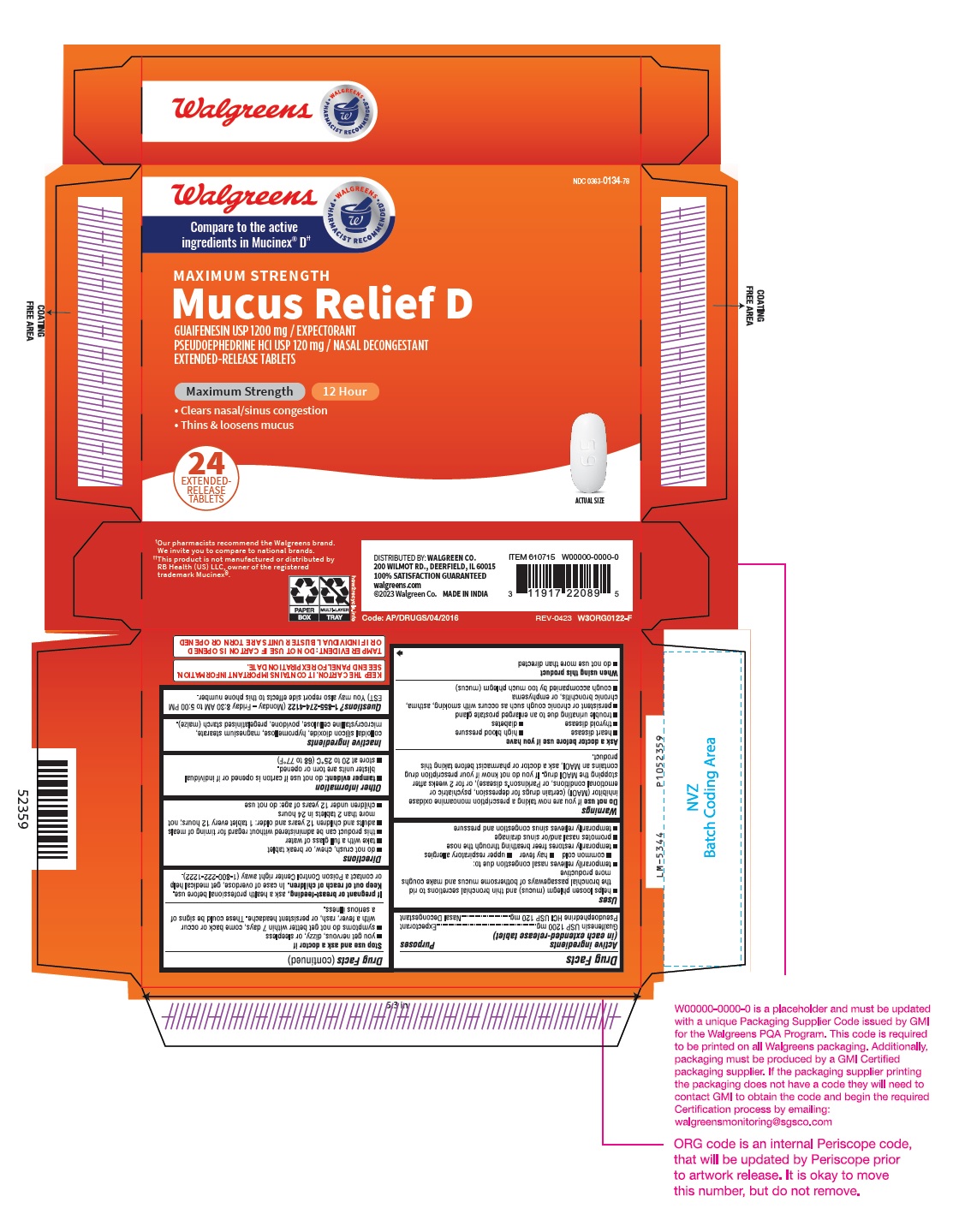 DRUG LABEL: Guaifenesin and Pseudoephedrine HCl
NDC: 0363-0134 | Form: TABLET, EXTENDED RELEASE
Manufacturer: WALGREEN CO.
Category: otc | Type: Human OTC Drug Label
Date: 20240420

ACTIVE INGREDIENTS: GUAIFENESIN 1200 mg/1 1; PSEUDOEPHEDRINE HYDROCHLORIDE 120 mg/1 1
INACTIVE INGREDIENTS: SILICON DIOXIDE; HYPROMELLOSE 2208 (15000 MPA.S); MAGNESIUM STEARATE; MICROCRYSTALLINE CELLULOSE 101; MICROCRYSTALLINE CELLULOSE 102; POVIDONE K25; POVIDONE K90; STARCH, CORN

Drug Facts

Active ingredients

(in each extended-release tablet)
Guaifenesin USP 1200 mg

Pseudoephedrine HCl USP 120 mg

Purposes

Expectorant

Nasal Decongestant

Uses

- helps loosen phlegm (mucus) and thin bronchial secretions to rid the bronchial passageways of bothersome mucus and make coughs more productive
- temporarily relieves nasal congestion due to:
  - common cold
  - hay fever
  - upper respiratory allergies
- temporarily restores freer breathing through the nose
- promotes nasal and/or sinus drainage
- temporarily relieves sinus congestion and pressure

Warnings

Do not use if you are now taking a prescription monoamine oxidase inhibitor (MAOI) (certain drugs for depression, psychiatric or emotional conditions, or Parkinson's disease), or for 2 weeks after stopping the MAOI drug. If you do not know if your prescription drug contains an MAOI, ask a doctor or pharmacist before taking this product.

Ask a doctor before use if you have

- heart disease
- high blood pressure
- thyroid disease
- diabetes
- trouble urinating due to an enlarged prostate gland
- persistent or chronic cough such as occurs with smoking, asthma, chronic bronchitis, or emphysema
- cough accompanied by too much phlegm (mucus)

When using this product

- do not use more than directed

Stop use and ask a doctor if

- you get nervous, dizzy, or sleepless
- symptoms do not get better within 7 days, come back or occur with a fever, rash, or persistent headache. These could be signs of a serious illness.

If pregnant or breast-feeding,

ask a health professional before use.

Keep out of reach of children.

In case of overdose, get medical help or contact a Poison Control Center right away (1-800-222-1222).

Directions

- do not crush, chew, or break tablet
- take with a full glass of water
- this product can be administered without regard for timing of meals
- adults and children 12 years and older: 1 tablet every 12 hours; not more than 2 tablets in 24 hours
- children under 12 years of age: do not use

Other information

- tamper evident: do not use if carton is opened or if individual blister units are torn or opened.
- store at 20 to 25°C (68 to 77°F)

Inactive ingredients

colloidal silicon dioxide, hypromellose, magnesium stearate, microcrystalline cellulose, povidone, pregelatinised starch (maize).

Questions?

1-855-274-4122 (Monday – Friday 8:30 AM to 5:00 PM EST) You may also report side effects to this phone number.

DISTRIBUTED BY: WALGREEN CO.
200 WILMOT RD., DEERFIELD, IL 60015
100% SATISFACTION GUARANTEED
walgreens.com
©2023 Walgreen Co.
Made in India
Code: AP/DRUGS/04/2016

PACKAGE LABEL-PRINCIPAL DISPLAY PANEL - 1200 mg/120 mg (24 Tablet Carton Label)

walgreens
Compare to the active
ingredients in Mucinex®D††
NDC 0363-0134-78
MAXIMUM STRENGTH
Mucus Relief D
GUAIFENESIN USP 1200 mg / EXPECTORANT
PSEUDOEPHEDRINE HCl USP 120 mg / NASAL DECONGESTANT
EXTENDED-RELEASE TABLETS
Maximum Strength 12 Hour
• Clears nasal/sinus congestion
• Thins & loosens mucus
24
EXTENDED-
RELEASE
TABLETS ACTUAL SIZE